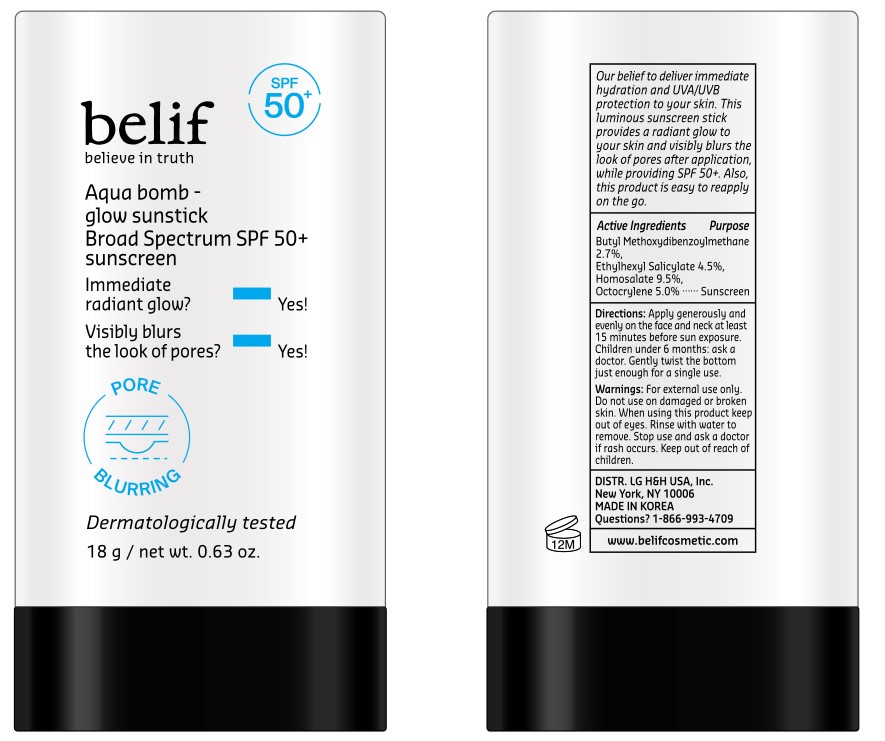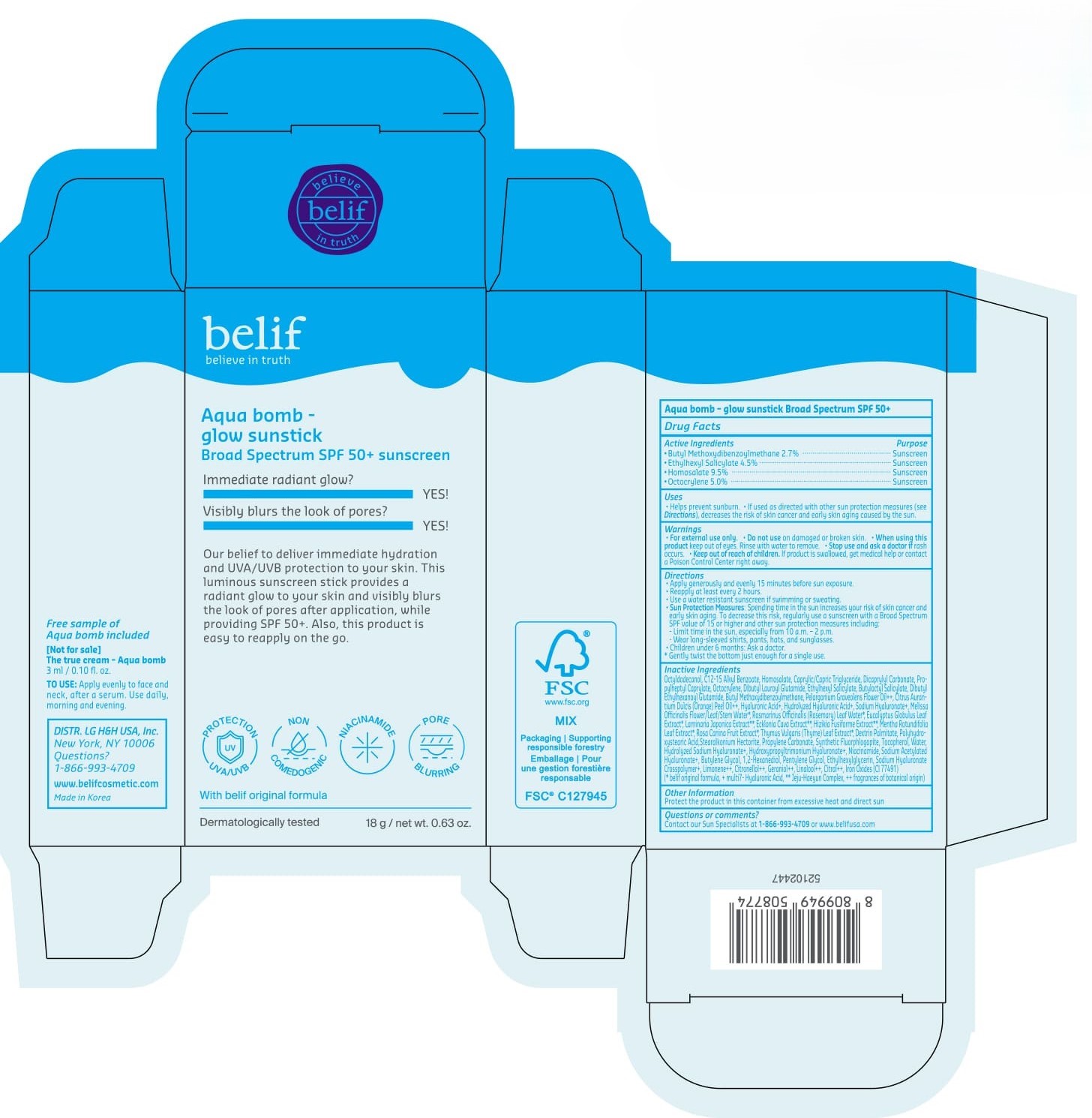 DRUG LABEL: belif Aqua bomb - glow sunstick SPF50
NDC: 53208-730 | Form: STICK
Manufacturer: LG H&H CO., LTD.
Category: otc | Type: HUMAN OTC DRUG LABEL
Date: 20250409

ACTIVE INGREDIENTS: AVOBENZONE 2.7 g/100 g; HOMOSALATE 9.5 g/100 g; OCTOCRYLENE 5 g/100 g; OCTISALATE 4.5 g/100 g
INACTIVE INGREDIENTS: CITRUS AURANTIUM DULCIS (ORANGE) PEEL OIL; BUTYLENE GLYCOL; PELARGONIUM GRAVEOLENS FLOWER OIL; STEARALKONIUM HECTORITE; ROSMARINUS OFFICINALIS (ROSEMARY) LEAF OIL; MENTHA X ROTUNDIFOLIA LEAF; PENTYLENE GLYCOL; ECKLONIA CAVA; LAMINARIA JAPONICA; DICAPRYLYL CARBONATE; PROPYLHEPTYL CAPRYLATE; BUTYLOCTYL SALICYLATE; POLYHYDROXYSTEARIC ACID (2300 MW); EUCALYPTUS GLOBULUS LEAF; C12-15 ALKYL BENZOATE; CITRAL; MAGNESIUM POTASSIUM ALUMINOSILICATE FLUORIDE; DEXTRIN PALMITATE (CORN; 20000 MW); ETHYLHEXYLGLYCERIN; DIBUTYL ETHYLHEXANOYL GLUTAMIDE; CAPRYLIC/CAPRIC TRIGLYCERIDE; TOCOPHEROL; ROSA CANINA FRUIT; NIACINAMIDE; THYMUS VULGARIS (THYME) LEAF; SODIUM ACETYLATED HYALURONATE; LIMONENE, (+)-; CITRONELLOL; GERANIOL; LINALOOL; DIBUTYL LAUROYL GLUTAMIDE; SODIUM HYALURONATE; PROPYLENE CARBONATE; HYALURONIC ACID; OCTYLDODECANOL; WATER; 1,2-HEXANEDIOL; CI 77491; SARGASSUM FUSIFORME; MELISSA OFFICINALIS FLOWERING TOP

Active Ingredients

Butyl Methoxydibenzolylmethane 2.7%

Ethylhexyl Salicylate 4.5%

Homosalate 9.5%

Octocrylene 5.0%

Purpose

Sunscreen

Uses

- Helps prevent sunburn.
- If used as directed with other sun protection measures (see Directions), decreases the risk of skin cancer and early skin aging caused by the sun.

For external use only.

Do not use on damaged or broken skin

When using

When using this product keep out of eyes. Rinse with water to remove.

Stop use

Stop use and ask a doctor if rash occurs.

Keep out of reach of children

DOSAGE AND ADMINISTRATION

If product is swallowed, get medical help or contact a Poison Control Center right away.

Directions

- Apply generously and evenly 15 minutes before sun exposure.
- Reapply at least every 2 hours.
- Use a water resistant sunscreen if swimming or sweating.
- Sun Protection Measure: Spending time in the sun increases your risk of skin cancer and early skin aging. To decrease this risk, regularly use a sunscreen with a Broad Spectrum SPF value of 15 or higher and other sun protection measures including:
  - Limit time in the sun, especially from 10 a.m.-2 p.m.
  - Wear long-sleeved shirts, pants, hats, and sunglasses.
- Children under 6 months: Ask a doctor.

*Gently twist the bottom just enough for a single use.

Inactive Ingredients

Octyldodecanol, C12-15 Alkyl Benzoate, Caprylic/Capric Triglyceride, Dicaprylyl Carbonate, Propylheptyl Caprylate, Dibutyl Lauroyl Glutamide, Butyloctyl Salicylate, Dibutyl Ethylhexanoyl Glutamide, Pelargonium Graveolens Flower Oil++, Citrus Aurantium Dulcis (Orange) Peel Oil++, Hyaluronic Acid+, Hydrolyzed Hyaluronic Acid+, Sodium Hyaluronate+, Melissa Officinalis Flower/Leaf/Stem Water*, Rosmarinus Officinalis (Rosemary) Leaf Water*, Eucalyptus Globulus Leaf Extract*, Laminaria Japonica Extract**, Ecklonia Cava Extract**, Hizikia Fusiforme Extract**, Mentha Rotundifolia Leaf Extract*, Rosa Canina Fruit Extract*, Thymus Vulgaris (Thyme) Leaf Extract*, Dextrin Palmitate, Polyhydroxystearic Acid, Stearalkonium Hectorite, Propylene Carbonate, Synthetic Fluorphlogopite, Tocopherol, Water, Hydrolyzed Sodium Hyaluronate+, Hydroxypropyltrimonium Hyaluronate+, Niacinamide, Sodium Acetylated Hyaluronate+, Butylene Glycol, 1,2-Hexanediol, Pentylene Glycol, Ethylhexylglycerin, Sodium Hyaluronate Crosspolymer+, Limonene++, Citronellol++, Geraniol++, Linalool++, Citral++, Iron Oxides (CI 77491)

*belif original formula

+multi7- Hyaluronic Acid

** Jeju-Haeyun Complex

++ frangrances of botanical origin

Other Information

Protect the product in this container from excessive heat and direct sun.

Questions or comments?

Contact our Sun Specialist at 1-866-993-4709 or www.belifusa.com